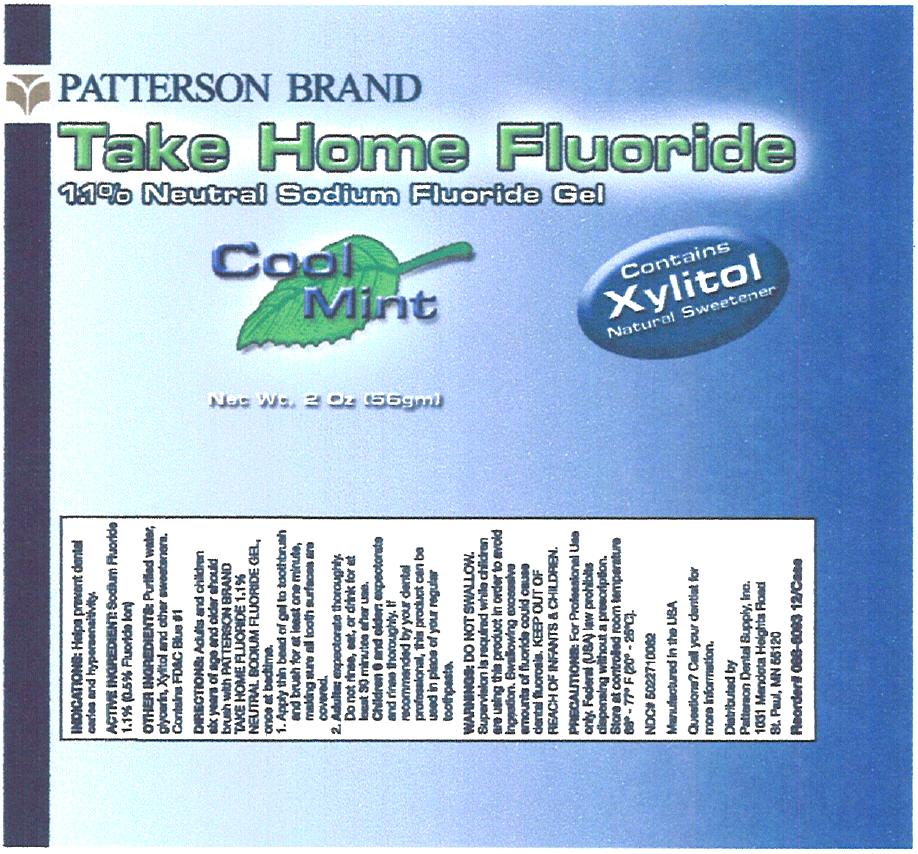 DRUG LABEL: Take Home Fluoride 
NDC: 50227-1006 | Form: GEL, DENTIFRICE
Manufacturer: Patterson Dental Supply Inc
Category: prescription | Type: HUMAN PRESCRIPTION DRUG LABEL
Date: 20120426

ACTIVE INGREDIENTS: Sodium Fluoride 5 mg/1 g
INACTIVE INGREDIENTS: Water; Anhydrous Citric Acid; Saccharin Sodium Dihydrate; Xylitol; Xanthan Gum; Glycerin

Take Home Fluoride 1.1% Neutral Sodium Fluoride Gel- Cool Mint

INDICATIONS

Helps prevent dental caries and hypersensitivity.

ACTIVE INGREDIENT

Sodium Fluoride 1.1% (0.5% Fluoride Ion)

OTHER INGREDIENTS

Purified water, glycerin, Xylitol and other sweeteners. Contains FD&C Blue #1

DIRECTIONS

Adults and children six years of age and older should brush with PATTERSON BRAND TAKE HOME FLUORIDE 1.1% NEUTRAL SODIUM FLUORIDE GEL, once at bedtime.

1. Apply thin bead of gel to toothbrush and brush for at least one minute making sure all tooth surfaces are covered.
2. Adults: expectorate thoroughly. Do not rinse, eat, or drink for at least 30 minutes after use.
  Children 6 and older: expectorate and rinse thoroughly. If recommended by your dental professional, this product can be used in place of your regular toothpaste.

WARNINGS

DO NOT SWALLOW. Supervision is required while children are using this product in order to avoid ingestion. Swallowing excessive amounts of fluoride could cause dental fluorosis. KEEP OUT OF REACH OF INFANTS & CHILDREN.

PRECAUTIONS

For Professional Use only. Federal (USA) law prohibits dispensing without a prescription. Store at controlled room temperature 68° -77° F (20° - 25°C).

NDC# 5022710062

Manufactured in the USA

Questions? Call your dentist for more information.

Distributed by
Patterson Dental Supply, Inc.
1031 Mendota Heights Road
St. Paul, MN 55120

Reorder# 088-6093 12/Case

PRINCIPAL DISPLAY PANEL - 56 gm Tube Label

PATTERSON BRAND

Take Home Fluoride
1.1% Neutral Sodium Fluoride Gel

Cool
Mint

Contains
Xylitol
Natural Sweetener

Net Wt. 2 Oz (56gm)